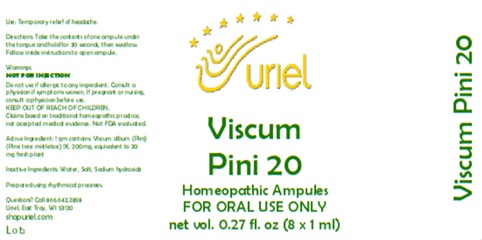 DRUG LABEL: Viscum Pini 20
NDC: 48951-9318 | Form: LIQUID
Manufacturer: Uriel Pharmacy Inc.
Category: homeopathic | Type: HUMAN OTC DRUG LABEL
Date: 20251210

ACTIVE INGREDIENTS: VISCUM ALBUM FRUITING TOP 1 [hp_X]/1 mL
INACTIVE INGREDIENTS: SODIUM HYDROXIDE; WATER; SODIUM CHLORIDE

Viscum Pini 20

PURPOSE

Use: Temporary relief of headache.

INDICATIONS AND USAGE

FOR ORAL USE ONLY

DOSAGE AND ADMINISTRATION

Directions: Take the contents of one ampule under the tongue and hold for 30 seconds, then swallow. Follow inside instructions to open ampule.

Active Ingredient: 1 gm contains: Viscum album (Pini) (Pine tree mistletoe) 1X, 200mg, equivalent to 20 mg fresh plant

Inactive Ingredients: Water, Salt, Sodium hydroxide

Prepared using rhythmical processes.

KEEP OUT OF REACH OF CHILDREN.

Warnings:
NOT FOR INJECTION
Do not use if allergic to any ingredient. Consult a physician if symptoms worsen. If pregnant or nursing, consult a physician before use.
Claims based on traditional homeopathic practice, not accepted medical evidence. Not FDA evaluated.

QUESTIONS

Questions? Call 866.642.2858 Uriel, East Troy, WI 53120 shopuriel.com Lot: